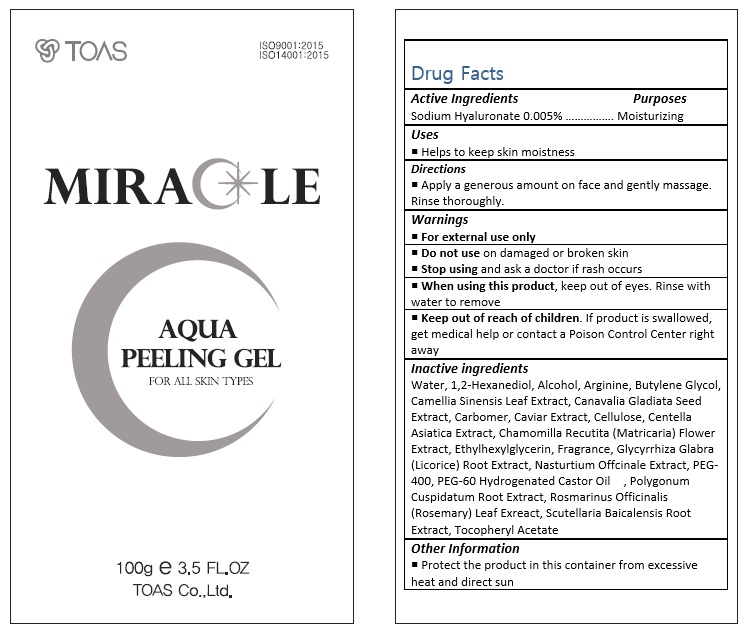 DRUG LABEL: Miracle Aqua Peeling
NDC: 72557-001 | Form: GEL
Manufacturer: TOAS Co., Ltd.
Category: otc | Type: HUMAN OTC DRUG LABEL
Date: 20180920

ACTIVE INGREDIENTS: HYALURONATE SODIUM 0.005 g/100 g
INACTIVE INGREDIENTS: WATER; 1,2-HEXANEDIOL; ALCOHOL; ARGININE; BUTYLENE GLYCOL; GREEN TEA LEAF; CARBOXYPOLYMETHYLENE; CAVIAR, UNSPECIFIED; POLYETHYLENE GLYCOL 400

Drug Facts

ACTIVE INGREDIENT

Sodium Hyaluronate 0.005%

PURPOSE

Moisturizing

INDICATIONS AND USAGE

Helps to keep skin moistness

DOSAGE AND ADMINISTRATION

Apply a generous amount on face and gently massage.
Rinse thoroughly.

WARNINGS

For external use only.
Do not use on damaged or broken skin.
When using this product, keep out of eyes. Rinse with water to remove.
Stop using and ask a doctor if rash occurs.

KEEP OUT OF REACH OF CHILDREN

Keep out of reach of the children. If product is swallowed, get medical help or contact a poison control center right away.

INACTIVE INGREDIENT

Water, 1,2-Hexanediol, Alcohol, Arginine, Butylene Glycol, Camellia Sinensis Leaf Extract, Canavalia Gladiata Seed Extract, Carbomer, Caviar Extract, Cellulose, Centella Asiatica Extract, Chamomilla Recutita (Matricaria) Flower Extract, Ethylhexylglycerin, Fragrance, Glycyrrhiza Glabra (Licorice) Root Extract, Nasturtium Offcinale Extract, PEG-400, PEG-60 Hydrogenated Castor Oil , Polygonum Cuspidatum Root Extract, Rosmarinus Officinalis (Rosemary) Leaf Exreact, Scutellaria Baicalensis Root Extract, Tocopheryl Acetate